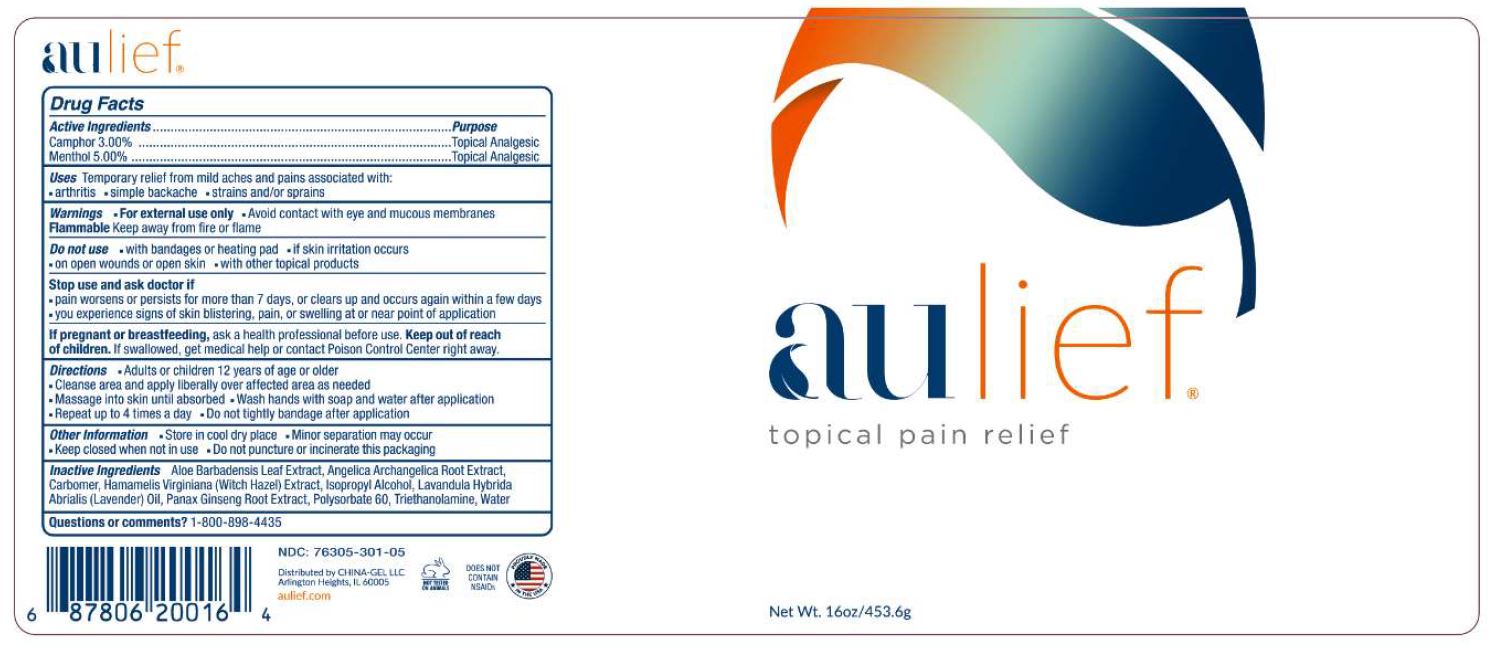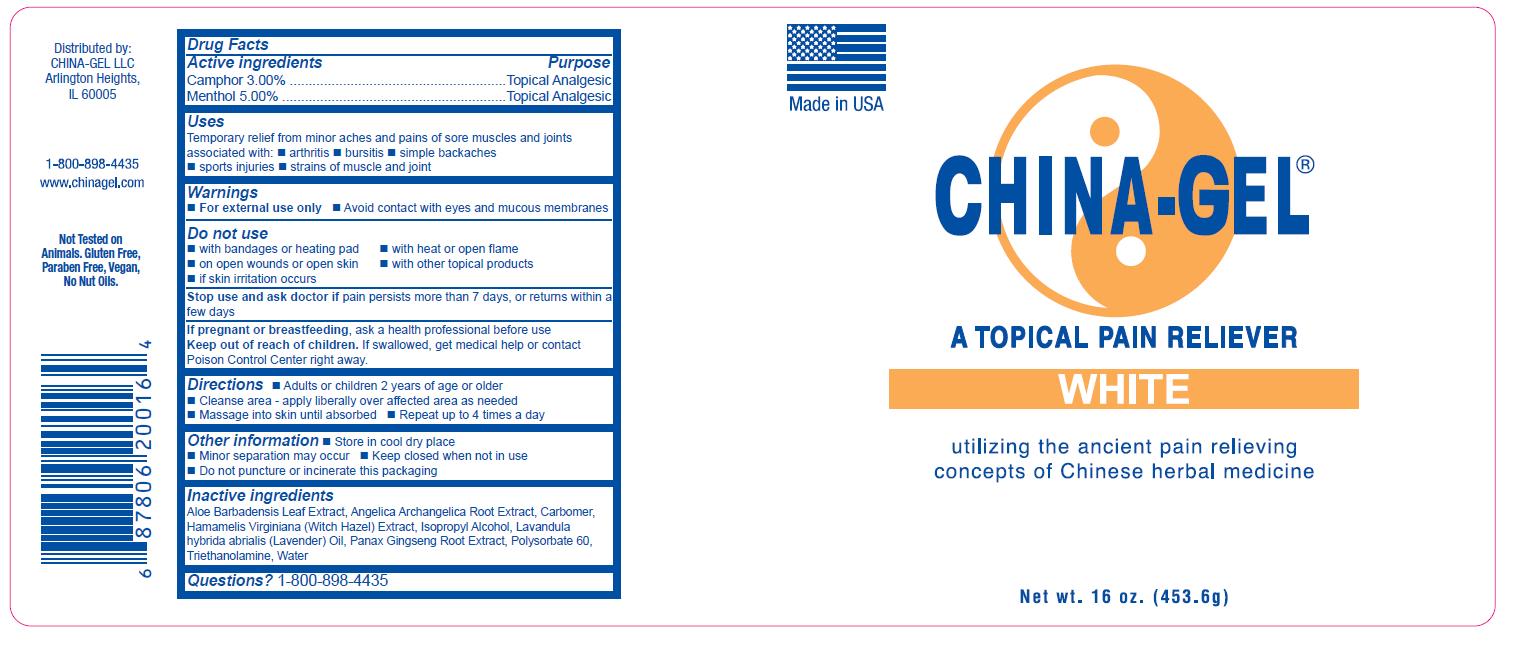 DRUG LABEL: China-Gel
NDC: 76305-301 | Form: CREAM
Manufacturer: China-Gel, LLC
Category: otc | Type: HUMAN OTC DRUG LABEL
Date: 20251104

ACTIVE INGREDIENTS: MENTHOL 50 mg/1 g; CAMPHOR (SYNTHETIC) 30 mg/1 g
INACTIVE INGREDIENTS: WATER; HAMAMELIS VIRGINIANA LEAF; ASIAN GINSENG; ALOE VERA LEAF; ANGELICA ARCHANGELICA ROOT; CARBOMER HOMOPOLYMER TYPE C; TROLAMINE; ISOPROPYL ALCOHOL; POLYSORBATE 60; LAVANDIN OIL

China Gel - White

Active Ingredients

Camphor 3.00%

Menthol 5.00%

Purpose

Topical Analgesic

Topical Analgesic

Uses

Temporary relief from minor aches and pains of sore muscles and joints associated with:

- arthritis
- bursitis
- simple backaches
- sports injuries
- strains of muscle and joint

Warnings

- For external use only
- avoid contact with eyes and mucous membranes

Do Not Use

- with bandages or heating pad
- on open wounds or open skin
- if skin irritation occurs
- with heat or open flame
- with other topical products

Stop use and ask doctor if

pain persists more than 7 days, or returns within a few days.

If pregnant or breastfeeding,

ask a health professional before use.

Keep out of reach of children.

If swallowed, get medical help or contact Poison Control Center right away.

Directions

- Adults or children 2 years of age or older
- Cleanse area - apply liberally over affected area as needed
- Massage into skin until absorbed
- Repeat up to 4 times a day

Other information

- Store in a cool, dry place
- Minor separation may occur
- Keep closed when not in use
- Do not puncture or incinerate this packaging

Inactive Ingredients

Aloe Barbadensis Leaf Extract, Angelica Archangelica Root Extract, Carbomer, Hamarnelis Virginiana (Witch Hazel) Extract, Isopropyl Alcohol, Lavandula hybrida abrialis (Lavender) Oil, Panax Gingseng Root Extract, Polysorbate 60, Triethanolamine, Water

Questions?

1-800-898-4435

Principal Display Panel

Made in USA
CHINA-GEL®

A TOPICAL PAIN RELIEVER

WHITE

utilizing the ancient pain relieving concepts of Chinese herbal medicine

Net wt. 16 oz. (453.6g)

Principal - Aulief

aulief

topical pain relief

Net Wt. 16oz/453.6g